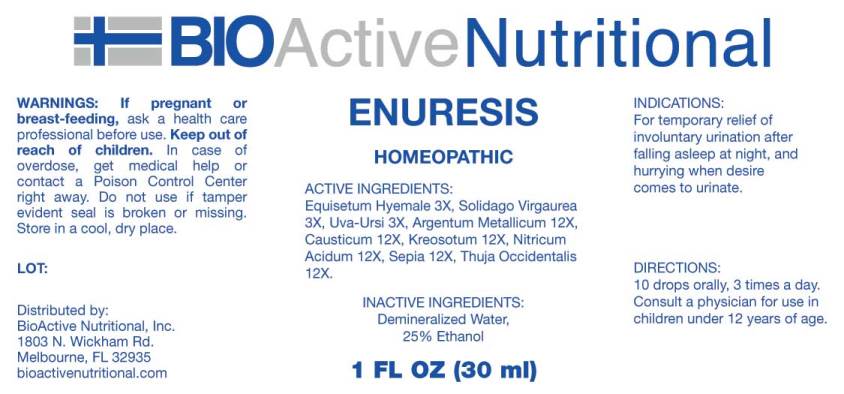 DRUG LABEL: Enuresis
NDC: 43857-0217 | Form: LIQUID
Manufacturer: BioActive Nutritional, Inc.
Category: homeopathic | Type: HUMAN OTC DRUG LABEL
Date: 20170614

ACTIVE INGREDIENTS: EQUISETUM HYEMALE 3 [hp_X]/1 mL; SOLIDAGO VIRGAUREA FLOWERING TOP 3 [hp_X]/1 mL; ARCTOSTAPHYLOS UVA-URSI LEAF 3 [hp_X]/1 mL; SILVER 12 [hp_X]/1 mL; CAUSTICUM 12 [hp_X]/1 mL; WOOD CREOSOTE 12 [hp_X]/1 mL; NITRIC ACID 12 [hp_X]/1 mL; SEPIA OFFICINALIS JUICE 12 [hp_X]/1 mL; THUJA OCCIDENTALIS LEAFY TWIG 12 [hp_X]/1 mL
INACTIVE INGREDIENTS: WATER; ALCOHOL

Drug Facts:

ACTIVE INGREDIENTS:

Equisetum Hyemale 3X, Solidago Virgaurea 3X, Uva-Ursi 3X, Argentum Metallicum 12X, Causticum 12X, Kreosotum 12X, Nitricum Acidum 12X, Sepia 12X, Thuja Occidentalis 12X.

INDICATIONS:

For temporary relief of involuntary urination after falling asleep at night, and hurrying when desire comes to urinate.

WARNINGS:

If pregnant or breast-feeding, ask a health care professional before use.

Keep out of reach of children. In case of overdose, get medical help or contact a Poison Control Center right away.

Do not use if tamper evident seal is broken or missing. Store in a cool, dry place.

Keep out of reach of children. In case of overdose, get medical help or contact a Poison Control Center right away.

DIRECTIONS:

10 drops orally, 3 times a day. Consult a physician for use in children under 12 years of age.

INDICATIONS:

For temporary relief of involuntary urination after falling asleep at night, and hurrying when desire comes to urinate.

INACTIVE INGREDIENTS:

Demineralized Water, 25% Ethanol

QUESTIONS:

Distributed by:

BioActive Nutritional, Inc.

1803 N. Wickham Rd.

Melbourne, FL 32935

bioactivenutritional.com

PACKAGE LABEL DISPLAY:

BioActive Homeopathic

ENURESIS

HOMEOPATHIC

1 FL OZ (30 ml)